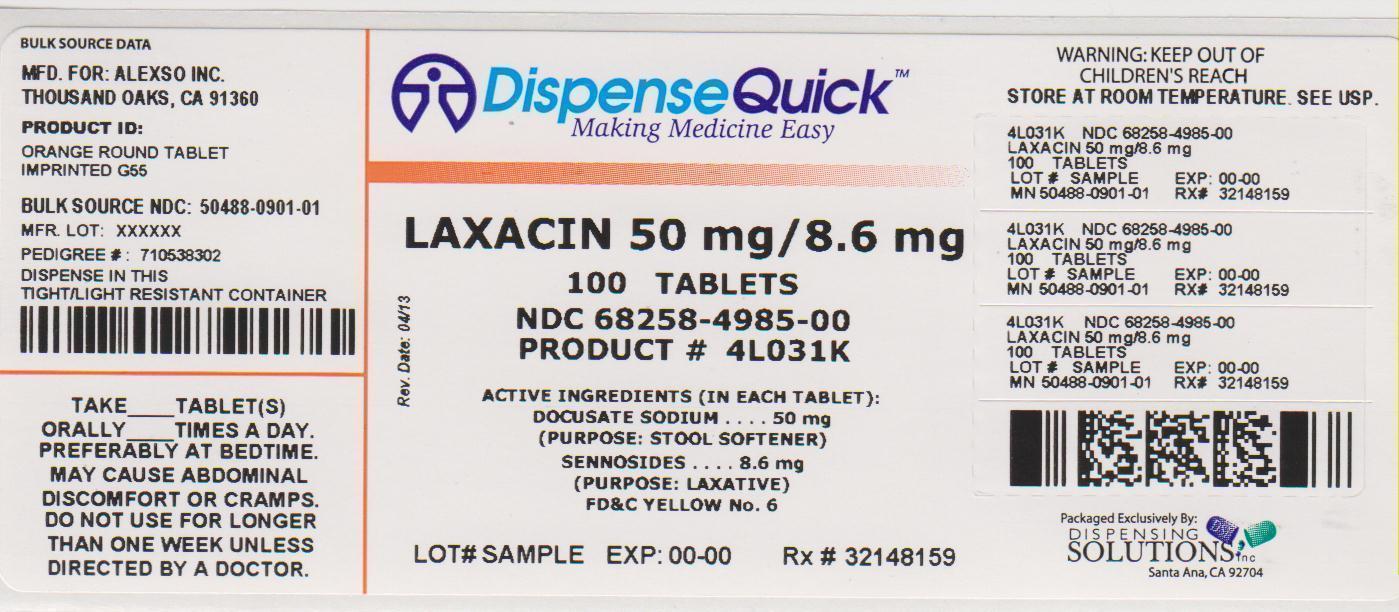 DRUG LABEL: Laxacin
NDC: 68258-4985 | Form: TABLET
Manufacturer: Dispensing Solutions, Inc.
Category: otc | Type: HUMAN OTC DRUG LABEL
Date: 20130712

ACTIVE INGREDIENTS: DOCUSATE SODIUM 50 mg/1 1; SENNOSIDES A AND B 8.6 mg/1 1
INACTIVE INGREDIENTS: CROSCARMELLOSE SODIUM; D&C YELLOW NO. 10; DEXTROSE; ANHYDROUS DIBASIC CALCIUM PHOSPHATE; FD&C YELLOW NO. 6; HYPROMELLOSES; MAGNESIUM STEARATE; CELLULOSE, MICROCRYSTALLINE; POLYETHYLENE GLYCOLS; SODIUM BENZOATE; STEARIC ACID; TITANIUM DIOXIDE

Laxacin
Laxative Plus Stool Softener

Active ingredient

Docusate Sodium 50 mg

Sennosides 8.6 mg

Purpose

Stool Softener

Laxative

Uses

- relieves occasional constipation (irregularity)
- generally produces a bowel movement in 6-12 hours

Warnings

Do not use

- if you are now taking mineral oil, unless directed by a doctor
- laxative products for longer than 1 week unless directed by a doctor

Ask a doctor before use if you have

- stomach pain
- nausea
- vomiting
- noticed a sudden change in bowel habits that continues over a period of 2 weeks

Stop use and ask a doctor if you have rectal bleeding or fail to have a bowel movement after use of a laxative.
These may indicate a serious condition.

If pregnant or breast feeding, ask a health professional before use.

Keep Out of Reach of Children

In case of overdose, get medical help or contact a Poison Control Center right away.

LOT#

Exp. Date:

Directions

- take preferably at bedtime or as directly by a doctor

age | starting dose | maximum dose
adults and children 12 years and older | 2 tablets once a day | 4 tablets twice a day

Other information

- Each tablet contains: Calcium 20 mg
- Each tablet contains: Sodium 4 mg
- Store at room temperature
- Keep lid tightly closed in a dry place
- Do not use if imprinted safety seal under cap is broken or missing

Inactive ingredients

Croscarmellose Sodium, D&C Yellow #10, Dextrose, Dicalcium Phosphate, FD&C Yellow #6, Hypromelose, Magnesium Stearate, Microcrystalline Cellulose, Polyethylene Glycol, Silica, Sodium Benzoate, Stearic Acid, Titanium Dioxide.

Questions? If you have any questions or comments, or to report an adverse event, please contact (480) 253-9761.

Manufactured for:
Alexso Inc.
Thousand Oaks, CA 91360

Package/Label Principal Display Panel

NDC 68258-4985-00